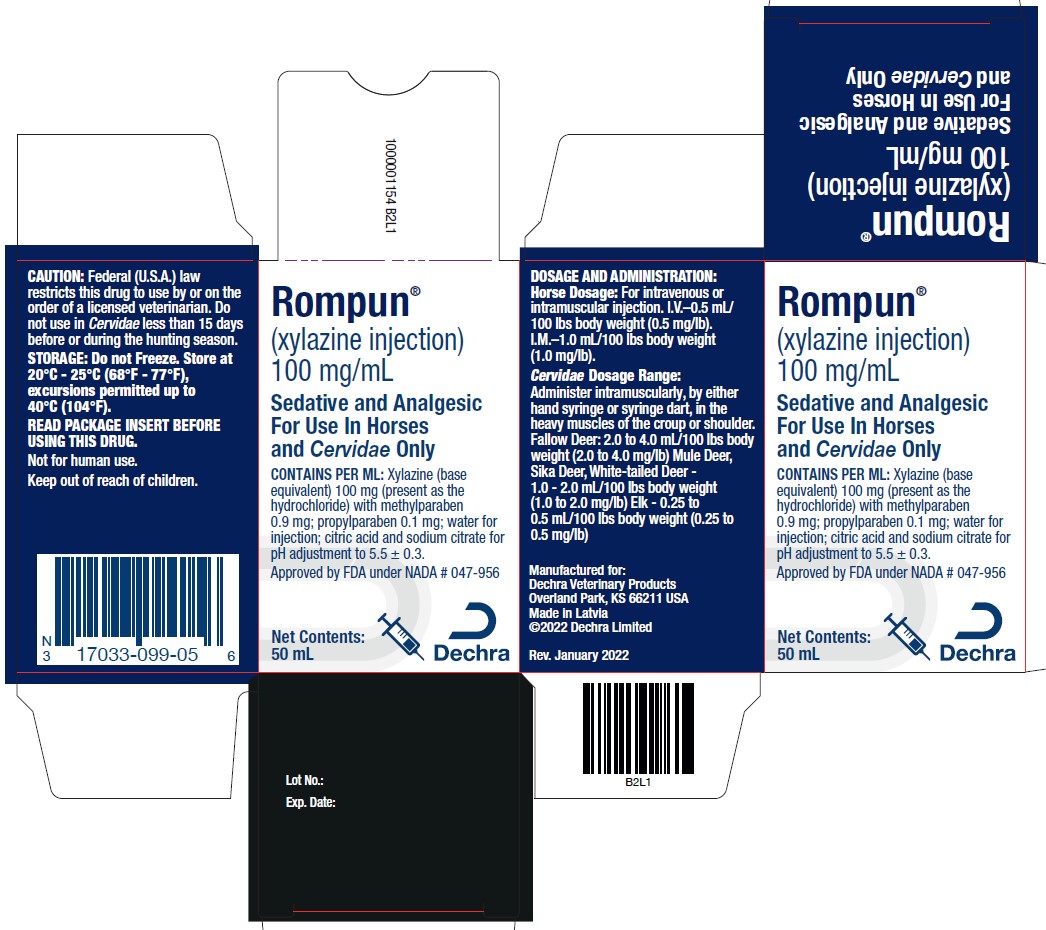 DRUG LABEL: Rompun
NDC: 17033-099 | Form: INJECTION, SOLUTION
Manufacturer: Dechra Vet Products, LLC
Category: animal | Type: PRESCRIPTION ANIMAL DRUG LABEL
Date: 20251219

ACTIVE INGREDIENTS: XYLAZINE 100 mg/1 mL

Rompun®
(xylazine injection)
100 mg/mL

Sedative and Analgesic For Use in Horses and Cervidae Only

DESCRIPTION

DESCRIPTION: Rompun (xylazine injection) is supplied in 50 mL multiple dose vials as a sterile solution. Each mL contains 100 mg Rompun (xylazine base equivalent); 0.9 mg methylparaben; 0.1 mg propylparaben; water for injection; citric acid and sodium citrate for pH adjustment to 5.5 + 0.3.

ACTIVE INGREDIENT:
xylazine hydrochloride (Equivalent to 10% base) | 11.4%
INERT INGREDIENTS: | 88.6% 100.0%

CAUTION: Federal (U.S.A.) law restricts this drug to use by or on the order of a licensed veterinarian. Do not use in Cervidae less than 15 days before or during the hunting season.

CLINICAL PHARMACOLOGY

PHARMACOLOGY: Rompun, a non-narcotic compound, is a sedative and analgesic as well as muscle relaxant. Its sedative and analgesic activity is related to central nervous system depression. Its muscle-relaxant effect is based on inhibition of the intraneural transmission of impulses in the central nervous system. The principal pharmacological activities develop within 10 to 15 minutes after intramuscular injection, and within 3 to 5 minutes following intravenous administration in horses.

A sleeplike state, the depth of which is dose-dependent, is usually maintained for 1 to 2 hours, while analgesia lasts from 15 to 30 minutes. The centrally-acting muscle relaxant effect causes relaxation of the skeletal musculature, complementing sedation and analgesia.

In horses and Cervidae under the influence of Rompun the respiratory rate is reduced as in natural sleep. Following treatment with Rompun the heart rate is decreased and a transient change in the conductivity of the cardiac muscle may occur, as evidenced by a partial atrioventricular block. This resembles the atrioventricular block often observed in normal horses.^(1, 2, 3, 4) Although a partial A-V block may occasionally occur following intramuscular injection of Rompun (xylazine injection), the incidence is less than when it is administered intravenously. Intravenous administration of Rompun (xylazine injection) causes a transient rise in blood pressure, followed by a slight decrease.

Rompun has no effect on blood clotting time or other hematologic parameters.

INDICATIONS AND USAGE

INDICATIONS: Rompun (xylazine injection) should be used in horses and Cervidae (Fallow Deer, Mule Deer, Sika Deer, White-Tailed Deer and Elk) when it is desirable to produce a state of sedation accompanied by a shorter period of analgesia.

Horses: Rompun (xylazine injection) has been used successfully as follows:

1. Diagnostic procedures–oral and ophthalmic examinations, abdominal palpation, rectal palpation, vaginal examination, catheterization of the bladder and radiographic examinations.
2. Orthopedic procedures, such as application of casting materials and splints.
3. Dental procedures.
4. Minor surgical procedures of short duration such as debridement, removal of cutaneous neoplasms and suturing of lacerations.
5. To calm and facilitate handling of fractious animals.
6. Therapeutic medication for sedation and relief of pain following injury or surgery.
7. Major surgical procedures:
  1. When used as a preanesthetic to general anesthesia.
  2. When used in conjunction with local anesthetics.

Cervidae: Rompun (xylazine injection) may be used for the following:

1. To calm and facilitate handling of fractious animals.
2. Diagnostic procedures.
3. Minor surgical procedures.
4. Therapeutic medication for sedation and relief of pain following injury or surgery.
5. As a preanesthetic to local anesthesia.
  Rompun at the recommended dosages can be used in conjunction with local anesthetics, such as procaine or lidocaine.

DOSAGE AND ADMINISTRATION:

1. Horse Dosage:
Intravenously–0.5 mL/100 lbs body weight (0.5 mg/lb)
Intramuscularly–1.0 mL/100 lbs body weight (1.0 mg/lb)
Following injection of Rompun (xylazine injection), the animal should be allowed to rest quietly until the full effect has been reached. These dosages produce sedation which is usually maintained for 1 to 2 hours, and analgesia which lasts for 15 to 30 minutes.
2. Preanesthetic to Local Anesthesia: Rompun at the recommended dosages can be used in conjunction with local anesthetics, such as procaine or lidocaine.
3. Preanesthetic to General Anesthesia: Rompun at the recommended dosage rates, produces an additive effect to central nervous system depressants such as pentobarbital sodium, thiopental sodium and thiamylal sodium. Therefore, the dosage of such compounds should be reduced and administered to the desired effect. In general, only 1/3 to 1/2 of the calculated dosage of the barbiturates will be needed to produce a surgical plane of anesthesia. Post-anesthetic or emergence excitement has not been observed in animals preanesthetized with Rompun. Rompun has been used successfully as a preanesthetic agent for pentobarbital sodium, thiopental sodium, thiamylal sodium, nitrous oxide, ether, halothane, glyceryl guaiacolate and methoxyflurane anesthesia.
4. Cervidae Dosage: Administer intramuscularly, either by hand syringe or syringe dart, in the heavy muscles of the croup or shoulder

Cervidae Dosage Range:
Fallow Deer (Dama dama) - 2.0 to 4.0 mL/100 lbs body weight (2.0 to 4.0 mg/lb).
Mule Deer (Odocoileus hemionus) - 1.0 to 2.0 mL/100 lbs body weight (1.0 to 2.0 mg/lb).
Sika Deer (Cervus nippon) - 1.0 to 2.0 mL/100 lbs body weight (1.0 to 2.0 mg/lb).
White-Tailed Deer (Odocoileus virginianus) - 1.0 to 2.0 mL/100 lbs body weight (1.0 to 2.0 mg/lb).
Elk (Cervus canadensis) - 0.25 to 0.5 mL/100 lbs body weight (0.25 to 0.5 mg/lb).

Following injection of Rompun the animal should be allowed to rest quietly until the full effect has been reached.

These dosages produce sedation which is usually maintained for 1 to 2 hours and analgesia which lasts for 15 to 30 minutes.

Use within 30 days of first puncture and puncture a maximum of 20 times. Any product remaining after 20 punctures or more than 30 days after initial puncture should be discarded.

ADVERSE REACTIONS

SIDE EFFECTS: Rompun (xylazine injection), in horses and Cervidae, used at recommended dosage levels may occasionally cause slight muscle tremors, bradycardia with partial A-V heart block and a reduced respiratory rate. Movement in response to sharp auditory stimuli may be observed. In horses, sweating, rarely profuse, has been reported following administration. In Cervidae, salivation, various vocalizations (bellowing, bleating, groaning, grunting, snoring) on expiration, audible grinding of molar teeth, protruding tongue and elevated temperatures have also been noted in some cases.

PRECAUTIONS

PRECAUTIONS: Careful consideration should be given before administering to horses and Cervidae with significantly depressed respiration, severe pathologic heart disease, advanced liver or kidney disease, severe endotoxic or traumatic shock, or stress conditions such as extreme heat, cold, high altitude or fatigue.

Do not use Rompun in conjunction with tranquilizers.

Analgesic effect is variable, and depth should be carefully assayed prior to surgical/clinical procedures. Variability of analgesia occurs most frequently at the distal extremities of horses and Cervidae.

Horses: Since an additive effect results from the use of Rompun and the barbiturate compounds, it should be used with caution with these central nervous system depressants. Products known to produce respiratory depression or apnea, such as thiamylal sodium, should be given at a reduced dosage and, when injected intravenously, should be administered slowly. When intravenous administration is desired, avoid perivascular injection in order to achieve the desired effect. Studies have shown negligible evidence of tissue irritation, however, following perivascular injection of xylazine.

Intracarotid Arterial Injection Should Be Avoided. As with many compounds, including tranquilizers, immediate violent seizures followed by collapse may result from inadvertent administration into the carotid artery. Although the reaction with Rompun (xylazine injection) is usually transient and recovery may be rapid and complete, special care should be taken to assure that the needle is in the jugular vein rather than the carotid artery.

Bradycardia and an arrhythmia in the form of incomplete atrioventricular block have been reported following Rompun (xylazine injection) administration. Although clinically the importance of this effect is questioned,^(1, 2, 3, 4) a standard dose of atropine given prior to or following Rompun (xylazine injection) will greatly decrease the incidence.

Sedation for transport is most successful if actual transportation is begun after the full effect of the drug has been reached and the animal's stability is maintained while standing. In addition, it should be noted that animals under the influence of Rompun (xylazine injection) can be aroused by noise or other stimuli and this may increase the risk of injury.

Cervidae: As in all ruminants, it is preferable to administer Rompun (xylazine injection) to fasted Cervidae as a safeguard against aspiration of food material into the lungs and/or bloat during deep sedation.

Care should be taken to administer Rompun (xylazine injection) in the heavy muscles of the croup or shoulder. Injections given subcutaneously, intraperitoneally or into fat deposits will give unpredictable results.

Intra-arterial injection should be avoided. As with many compounds, including tranquilizers, immediate violent seizures followed by collapse may result from inadvertent administration into an artery.

The animal should not be disturbed during induction or until the full effect of the drug has been reached which is usually 10 to 15 minutes following injection.

The usual time to initial effect of the drug is 2 to 5 minutes. The administrator of the drug should be fully cognizant of this interval prior to administration of drug to free ranging deer or elk, especially at night or in heavily wooded areas.

If the animal has been underdosed (faulty injection or miscalculation of weight) it is advisable to wait one hour before administering a second dose.

Adequate ventilation, especially in cages or crates, is mandatory; keep head and neck in position to insure patent air passage and to prevent aspiration of stomach contents.

During sedation animals should be prevented from assuming lateral recumbency. A sternal recumbent position is desirable.

While under the effects of Rompun (xylazine injection) the animal should be protected from an extremely hot or cold environment. Efforts should be made to prevent patient from rising until almost complete recovery is attained.

The transportation of Cervidae given Rompun (xylazine injection) should be carefully monitored to prevent excessive struggling, injury or death.

Hyperthermic reactions may occur, especially if the subject is in a highly excited state when the drug is administered. Hosing the head and entire body with cold water has usually proven to be an effective deterrent.

The safety of Rompun (xylazine injection) has not been demonstrated in pregnant Cervidae. Avoid use during the breeding season.

Cervidae should be observed closely until all of the sedative effects of Rompun (xylazine injection) are gone.

Care should be taken at all times when administering Rompun (xylazine injection) to Cervidae. This is due to the method of administration (usually darting), the difficulty in estimating body weights and the accepted theory that wild animals are more unpredictable in their response to sedatives and analgesics than the domesticated species.

WARNINGS

Human Safety: Not for human use. Keep out of reach of children.

- Strictly avoid self-injection, oral intake and any contact with skin, eyes or mucosa.
- In the case of accidental contact wash exposed skin or eyes abundantly with water. If symptoms occur, seek medical advice.
- In the case of accidental oral intake or self-injection, seek the advice of a physician and show the package insert but DO NOT DRIVE.
- If pregnant women handle the product, special caution should be observed not to self-inject as uterine contractions and decreased fetal blood pressure may occur after accidental systemic exposure.
- Users with cardiovascular disease (for example, hypertension or ischemic heart disease) should take special precautions to avoid any exposure to this product.
- Caution should be exercised when handling sedated animals. Handling or any other sudden stimuli, including noise, may cause a defense reaction in an animal that appears to be heavily sedated.

Note to physician: Xylazine is an alpha2-adrenergic agonist with sedative, some analgesic and muscle relaxant properties. Symptoms after absorption may include dose-dependent respiratory depression, bradycardia, hypotension, a dry mouth, and hyperglycemia. Ventricular arrhythmias have also been reported.

The safety data sheet (SDS) contains more detailed occupational safety information. To report adverse reactions in users or to obtain a copy of the SDS for this product call Dechra at 1-(866)-933-2472.

For additional information about reporting adverse drug experiences for animal drugs, contact FDA at 1-888-FDA-VETS or http://www.fda.gov/reportanimalae.

Animal safety: This drug should not be administered to domestic food-producing animals. Do not use in horses intended for human consumption.

In Cervidae, occasional capture-associated deaths occur. Clinical trials reveal a mortality rate of approximately 3.5% attendant with the administration of xylazine.

HOW SUPPLIED

HOW SUPPLIED: Rompun (xylazine injection) 100 mg/mL Injection for intravenous or intramuscular use is available in 50 mL multiple dose vials.

STORAGE AND HANDLING

STORAGE: Do not Freeze. Store at 20°C - 25°C (68°F - 77°F), excursions permitted up to 40°C (104°F).

REFERENCES:

1. Detweiler, D.K.: "The Diagnosis and Significance of Cardiac Arrhythmias." Progress In Equine Practice. Edited by E.J. Catcott and J.F. Smithcors.
  American Veterinary Publications, Inc., Santa Barbara. California and Wheaton, Illinois, (1966), 280-281.
2. Glazier, D.B.: "Atrioventricular Heart Block." Irish Vet. J, Vol. 12, (1958), 194-198.
3. Holmes, J.R., Alps, B.J.: "Observations on Partial Atrioventricular Heart Block in the Horse." Can. Vet. J., Vol. 7, No. 12, (1966), 280-290.
4. Smetzer, D.L., Smith, C.R., Senta, T: "Second Degree Atrioventricular Block in the Horse." Am. J. Vet. Res., Vol. 30, No. 6, (1969), 933-946.

Manufactured for:
Dechra Veterinary Products
7015 College Boulevard, Suite 525
Overland Park, KS 66211 USA

Made in Latvia

Approved by FDA under NADA # 047-956

1000001151 B2L2

Rompun® is a registered trademark of Dechra Limited.
© 2022 Dechra Limited

Rev. January 2022

PRINCIPAL DISPLAY PANEL - 50 mL Bottle Carton

Rompun®
(xylazine injection)
100 mg/mL

Sedative and Analgesic
For Use In Horses
and Cervidae Only

CONTAINS PER ML: Xylazine (base
equivalent) 100 mg (present as the
hydrochloride) with methylparaben
0.9 mg; propylparaben 0.1 mg; water for
injection; citric acid and sodium citrate for
pH adjustment to 5.5 ± 0.3.

Approved by FDA under NADA # 047-956

Net Contents:
50 mL

Dechra